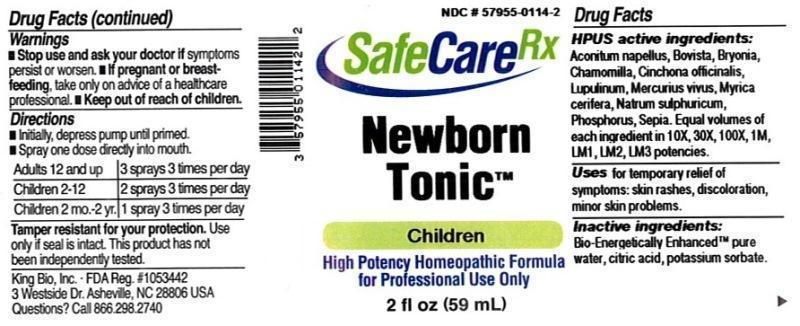 DRUG LABEL: Newborn Tonic
NDC: 57955-0114 | Form: LIQUID
Manufacturer: King Bio Inc.
Category: homeopathic | Type: HUMAN OTC DRUG LABEL
Date: 20150319

ACTIVE INGREDIENTS: ACONITUM NAPELLUS 10 [hp_X]/59 mL; LYCOPERDON UTRIFORME FRUITING BODY 10 [hp_X]/59 mL; BRYONIA ALBA ROOT 10 [hp_X]/59 mL; MATRICARIA RECUTITA 10 [hp_X]/59 mL; CINCHONA OFFICINALIS BARK 10 [hp_X]/59 mL; HOPS 10 [hp_X]/59 mL; MERCURY 10 [hp_X]/59 mL; MORELLA CERIFERA ROOT BARK 10 [hp_X]/59 mL; SODIUM SULFATE 10 [hp_X]/59 mL; PHOSPHORUS 10 [hp_X]/59 mL; SEPIA OFFICINALIS JUICE 10 [hp_X]/59 mL
INACTIVE INGREDIENTS: WATER; ANHYDROUS CITRIC ACID; POTASSIUM SORBATE

Newborn Tonic™

ACTIVE INGREDIENT

Drug Facts__________________________________________________________________________________________________________

HPUS active ingredients: Aconitum napellus, Bovista, Bryonia, Chamomilla, Cinchona officinalis, Lupulinum, Mercurius vivus, Myrica cerifera, Natrum sulphuricum, Phosphorus, Sepia. Equal volumes of each ingredient in 10X, 30X, 100X, 1M, LM1, LM2, LM3 potencies.

INDICATIONS AND USAGE

Uses for temporary relief of symptoms: skin rashes, discoloration, minor skin problems.

Inactive Ingredients:

Bio-Energetically Enhanced™ pure water, citric acid and potassium sorbate.

Warnings

- Stop use and ask your doctor if symptoms persist or worsen.
- If pregnant or breast-feeding, take only on advice of a healthcare professional.

- Keep out of reach of children.

Directions

- Initially, depress pump until primed.
- Spray one dose directly into mouth.
- Adults 12 and up: 3 sprays 3 times per day.
- Children 2-12: 2 sprays 3 times per day.
- Children 2 mo-2yr: 1 spray 3 times per day.

OTHER SAFETY INFORMATION

Tamper resistant for your protection. Use only if safety seal is intact. This product has not been independently tested.

PURPOSE

Uses for temporary relief of symptoms:

- skin rashes
- discoloration
- minor skin problems